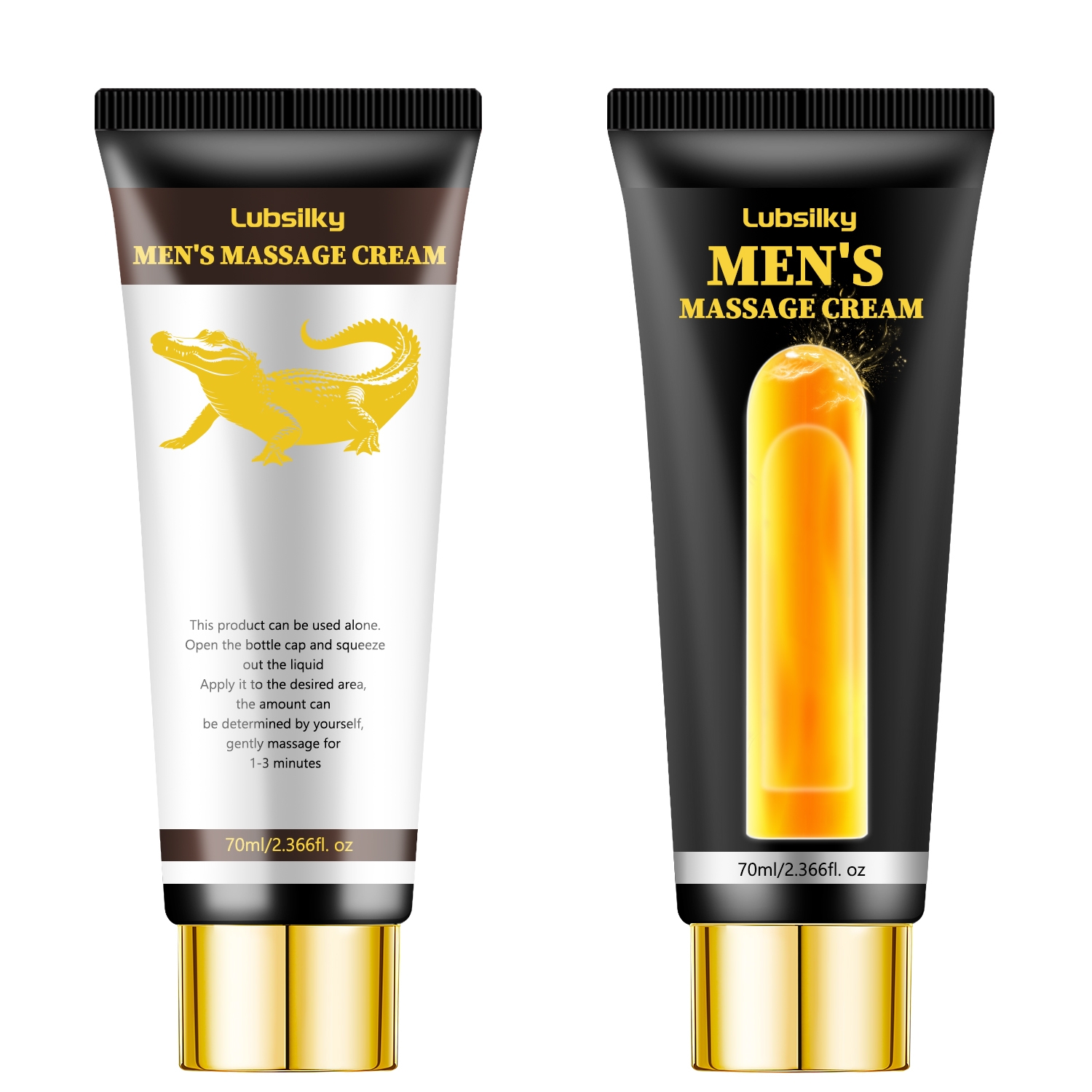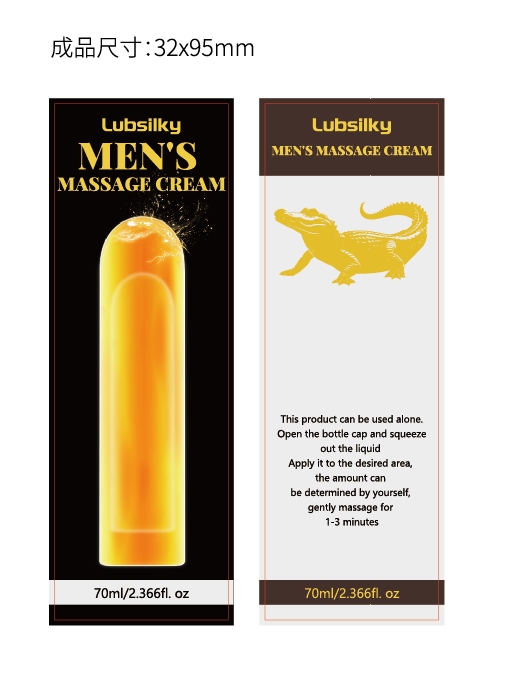 DRUG LABEL: Mens Massage Cream
NDC: 84025-301 | Form: CREAM
Manufacturer: Guangzhou Yanxi Biotechnology Co., Ltd
Category: otc | Type: HUMAN OTC DRUG LABEL
Date: 20250103

ACTIVE INGREDIENTS: GLYCERIN 5 mg/70 mL; NIACINAMIDE 3 mg/70 mL
INACTIVE INGREDIENTS: WATER

DOSAGE AND ADMINISTRATION

So easy to use, simply apply the appropriate amount of breast enhancement to a clean, private area and gently massage into ful absorption

WARNINGS

Keep out of children

INACTIVE INGREDIENT

Aqua

INDICATIONS AND USAGE

For daily skin care

Keep out of children

PURPOSE

Skin absorbs it easily, leaving skinhydrated, smooth, Deep moisturizing and nourishing skin, nongreasy, no sticky residue